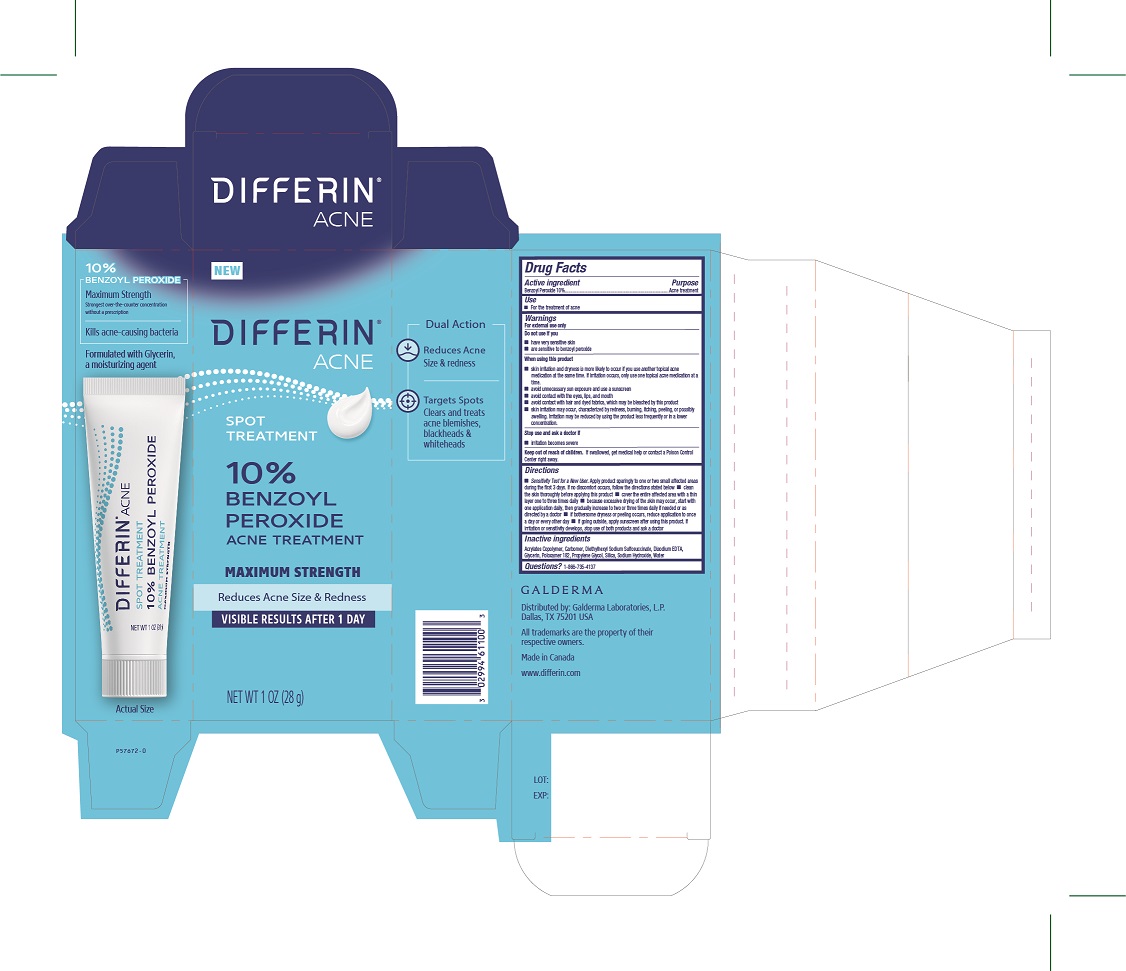 DRUG LABEL: Differin 10% BPO Acne Treatment
NDC: 0299-4611 | Form: SOLUTION
Manufacturer: Galderma Laboratories, L.P.
Category: otc | Type: HUMAN OTC DRUG LABEL
Date: 20240606

ACTIVE INGREDIENTS: Benzoyl Peroxide 10 g/100 g
INACTIVE INGREDIENTS: Butyl Acrylate/Methyl Methacrylate/Methacrylic Acid Copolymer (18000 Mw); Carbomer Homopolymer, Unspecified Type; Docusate Sodium; Edetate Disodium Anhydrous; Glycerin; Poloxamer 182; Propylene Glycol; Silicon Dioxide; Sodium Hydroxide; Water

Drug Facts

Active Ingredients

Benzoyl Peroxide 10%

Purpose

Acne treatment

Uses

For the treatment of acne

Warnings

For external use only.

Do not use if you
■ have very sensitive skin
■ are sensitive to benzoyl peroxide

When using this product
■ skin irritation and dryness is more likely to occur if you use another topical acne medication at the same time. If irritation occurs, only use one topical acne medication at a time.
■ avoid unnecessary sun exposure and use a sunscreen
■ avoid contact with the eyes, lips, and mouth
■ avoid contact with hair and dyed fabrics, which may be bleached by this product
■ skin irritation may occur, characterized by redness, burning, itching, peeling, or possibly swelling. Irritation may be reduced by using the product less frequently or in a lower concentration.

Stop use and ask a doctor if
■ irritation becomes severe.

Keep out of reach of children.
If swallowed, get medical help or contact a Poison Control Center right away.

Directions

• Sensitivity Test for a New User. Apply product sparingly to one or two small affected areas during the first 3 days. If no discomfort occurs, follow the directions stated below ■ clean the skin thoroughly before applying this product ■ cover the entire affected area with a thin layer one to three times daily ■ because excessive drying of the skin may occur, start with one application daily, then gradually increase to two or three times daily if needed or as directed by a doctor ■ if bothersome dryness or peeling occurs, reduce application to once a day or every other day ■ if going outside, apply sunscreen after using this product. If irritation or sensitivity develops, stop use of both products and ask a doctor

Inactive Ingredients

Acrylates Copolymer, Carbomer, Diethylhexyl Sodium Sulfosuccinate, Disodium EDTA, Glycerin, Poloxamer 182, Propylene Glycol, Silica, Sodium Hydroxide, Water

Questions or comments?

1-866-735-4137

QUESTIONS

Distributed by:

Galderma Laboratories, L.P.

Dallas, TX 75201
USA

All trademarks are the property of their respective owners

Made in Canada

www.differin.com

Principle Display Panel - 1 OZ (28 g) carton

NEW
DIFFERIN®
Acne
Spot
Treatment
10%
BENZOYL
PEROXIDE
Acne Treatment

MAXIMUM STRENGTH
Reduces Acne Size & Redness
VISIBLE RESULTS AFTER 1 DAY
NET WT 1 OZ (28 g)
P57672-0